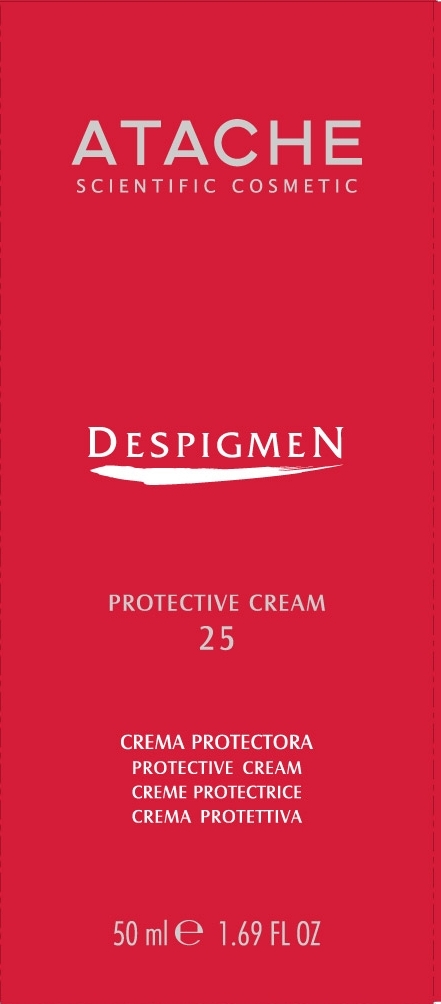 DRUG LABEL: DESPIGMEN PROTECTIVE 25
NDC: 75870-003 | Form: CREAM
Manufacturer: LABORATORIOS DE COSMETICA SCIENTIFICA AT
Category: otc | Type: HUMAN OTC DRUG LABEL
Date: 20110616

ACTIVE INGREDIENTS: OCTINOXATE 3 mL/50 mL; TITANIUM DIOXIDE 0.88 mL/50 mL
INACTIVE INGREDIENTS: WATER; TRIBEHENIN PEG-20 ESTERS; ABETIMUS SODIUM; JOJOBA OIL; BISOCTRIZOLE; GLYCERIN; DODECYL BENZOATE; ALPHA-TOCOPHEROL; ALUMINUM STEARATE; HYDROXYSTEARIC ACID; ALUMINUM OXIDE; EDETATE DISODIUM; PROPYLENE GLYCOL; XANTHAN GUM; PHENOXYETHANOL; METHYLPARABEN; BUTYLPARABEN; ETHYLPARABEN; PROPYLPARABEN

DESPIGMEN PROTECTIVE CREAM 25

DESCRIPTION

Protector that provides the latest in scientific cosmetics to prevent dark spots, protecting the skin from sun damage and aging.

Protection against UVA light is due to its state-of-the art "organo-mineral" solar filter.

Protection against UVB light occurs by a highly efficient inorganic filter.

Perfectly protected, the skin appear uniform, luminous, and free from shine.

INSTRUCTIONS FOR USE

Directions: Gently massage into the skin of the face, neck, decolletage, and hands 30 minutes before sun exposure.

WARNINGS

Warnings: For external use only. Keep out of reach of children. Avoid contact with eyes. Discontinue use if signs of irritation or rash appear.

ACTIVE INGREDIENTS:

OCTINOXATE 6% - sunscreen

TITANIUM DIOXIDE 1.75% - sunscreen

INACTIVE INGREDIENT

OTHER INGREDIENTS: AQUA, TRIBEHENIN PEG-20 ESTERS, OCTYLDODECYL MYRISTATE, HYDROGENATED POLYDECENE, SIMMONDSIA CHINENSIS OIL, METHYLENE BIS-BENZOTRIAZOLYL TETRAMETHYLBUTYLPHENOL, GLYCERIN, C12-15 ALKYLBENZOATE, CETEARYL ALCOHOL, DECYL GLUCOSIDE, TOPHENYL ACETATE, ALUMINUM STEARATE, POLYHYDROXYSTEARIC ACID, ALUMINIUM OXIDE, DISODIUM EDTA, PROPYLENE GLYCOL, XANTYAN GUM, PHENOXYETHANOL, METHYLPARABEN, BUTYLPARABEN, ETHYLPARABEN, PROPYLPARABEN.